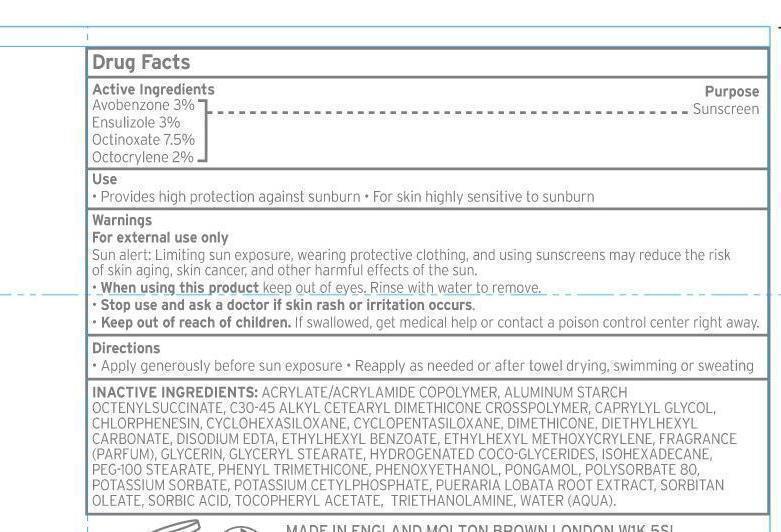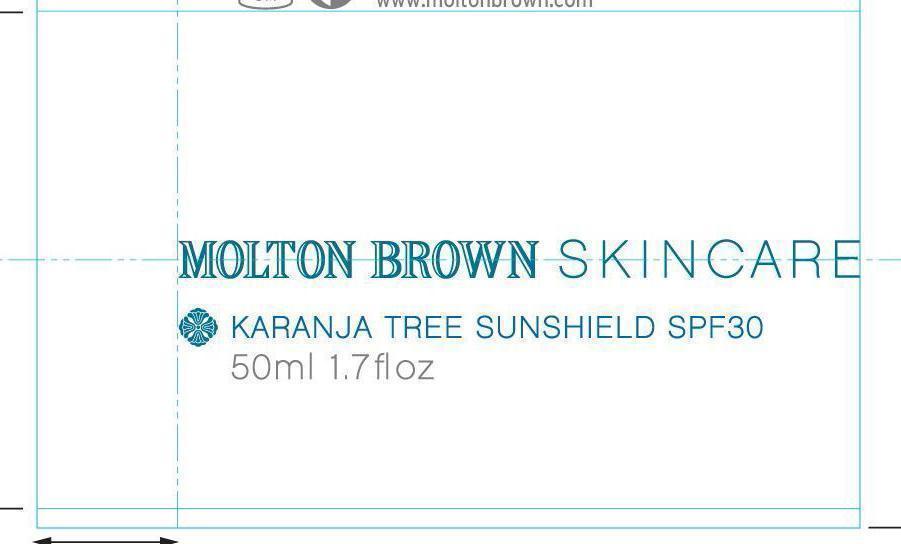 DRUG LABEL: Karanja Tree Sunshield SPF 30
NDC: 68814-128 | Form: CREAM
Manufacturer: Molton Brown LTD
Category: otc | Type: HUMAN OTC DRUG LABEL
Date: 20130404

ACTIVE INGREDIENTS: AVOBENZONE 3 g/100 mL; ENSULIZOLE 3 g/100 mL; OCTINOXATE 7.5 g/100 mL; OCTOCRYLENE 2 g/100 mL
INACTIVE INGREDIENTS: ALUMINUM STARCH OCTENYLSUCCINATE; CAPRYLYL GLYCOL; CHLORPHENESIN; CYCLOMETHICONE 6; CYCLOMETHICONE 5; DIMETHICONE; DIETHYLHEXYL CARBONATE; EDETATE DISODIUM; GLYCERIN; GLYCERYL MONOSTEARATE; ISOHEXADECANE; POLYOXYL 100 STEARATE; PHENYL TRIMETHICONE; PHENOXYETHANOL; POLYSORBATE 80; POTASSIUM SORBATE; POTASSIUM CETYL PHOSPHATE; SORBITAN MONOOLEATE; SORBIC ACID; TROLAMINE

Karanja Tree Sunshield SPF30

Active ingredients Purpose

Avobenzone 3% Sunscreen

Ensulizole 3% Sunscreen

Octinoxate 7.5% Sunscreen

Octocrylene 2% Sunscreen

Use

Provides high protection against sunburn - For skin highly sensitive to sunburn.

Keep out of reach of children. If swallowed, get medical help or contact a poison control center right away.

indications

Stop use and ask a doctor if skin rash or irritation occurs.

Warnings

For external use only.

Sun alert: Limiting sun exposure, wearing protective clothing, and using sunscreens may reduce the risk of skin aging, skin cancer and other harmful effects of the sun.

When using this product, keep out of eyes. Rinse with water to remove.

Directions

-Apply generously before sun exposure

-reapply as needed or after towel drying, swimming, or sweating.

Inactive ingredients

Acrylate/acrylamide copolymer, aluminum starch octenylsuccinate, C30-45 alkyl cetearyl dimethicone crosspolymer, caprylyl glycol, chlorphenesin, cyclohexasiloxane, cyclopentasiloxane, dimethicone, diethylhexyl carbonate, disodium EDTA, ethylhexyl benzoate, ethyhexyl methoxycrylene,fragrance (parfum), glycerin, glyceryl stearate, hydrogenated coco-glycerides, isohexadecane, Peg-100 stearate, phenyl trimethicone, phenoxyethanol, pongamal, polysorbate 80, potassium sorbate, potassium cetylphosphate, Pueraria Lobata root extract, Sorbitan oleate, sorbic acid, Tocopheryl acetate, triethanolamine, water (aqua).

PACKAGE LABEL

Molton Brown Skin Care
Karanja Tree Sunshield SPF30 50ml 1.7 fl oz